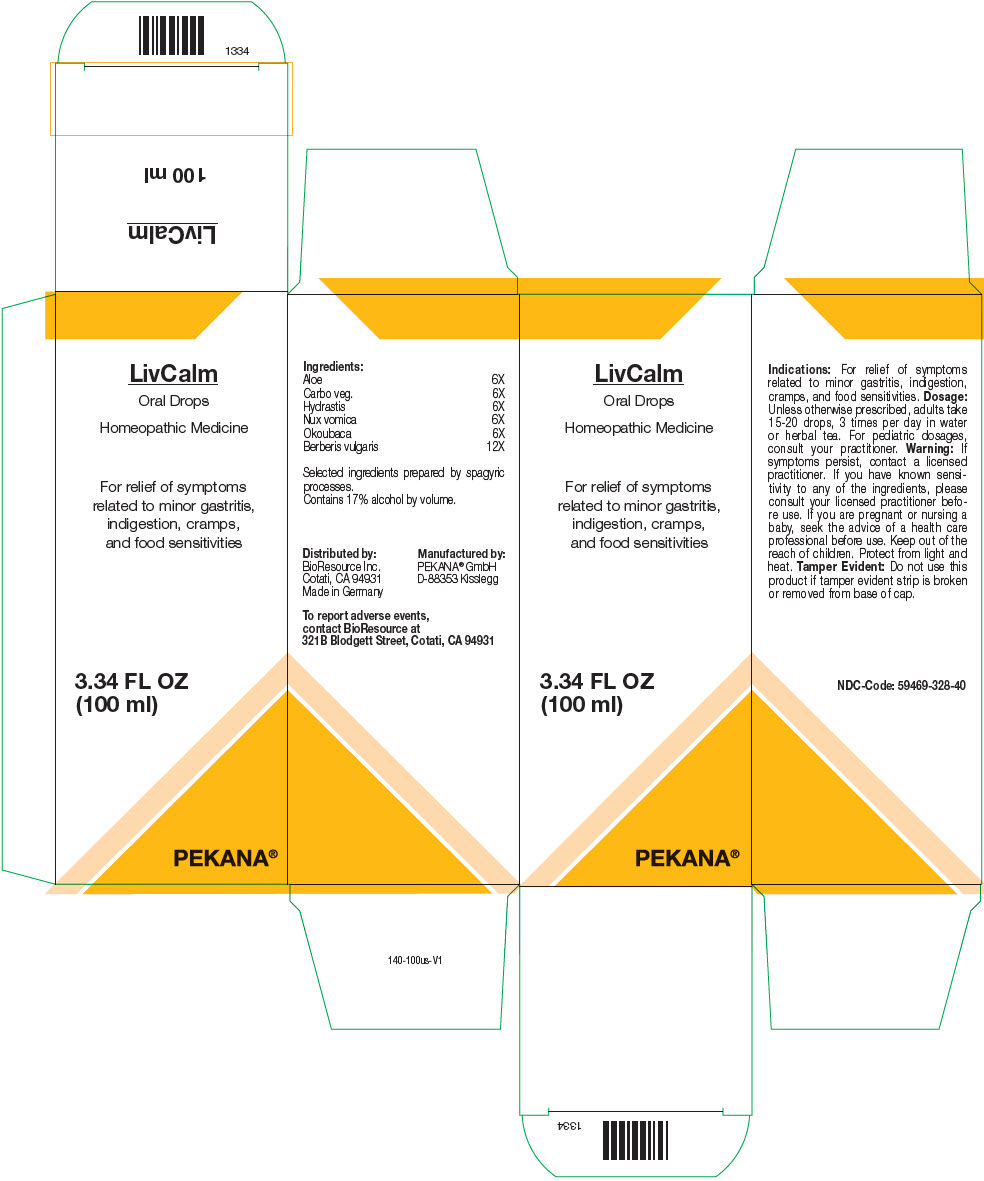 DRUG LABEL: LivCalm
NDC: 59469-328 | Form: SOLUTION/ DROPS
Manufacturer: PEKANA Natuheilmittel GmbH
Category: homeopathic | Type: HUMAN OTC DRUG LABEL
Date: 20221227

ACTIVE INGREDIENTS: ALOE FEROX LEAF 6 [hp_X]/100 mL; ACTIVATED CHARCOAL 6 [hp_X]/100 mL; GOLDENSEAL 6 [hp_X]/100 mL; STRYCHNOS NUX-VOMICA SEED 6 [hp_X]/100 mL; OKOUBAKA AUBREVILLEI BARK 6 [hp_X]/100 mL; BERBERIS VULGARIS ROOT BARK 12 [hp_X]/100 mL
INACTIVE INGREDIENTS: Water; Alcohol

LivCalm

ACTIVE INGREDIENT

Ingredients:
Aloe | 6X
Carbo veg. | 6X
Hydrastis | 6X
Nux vomica | 6X
Okoubaca | 6X
Berberis vulgaris | 12X

Selected ingredients prepared by spagyric processes.

INACTIVE INGREDIENT

Contains 17% alcohol by volume.

Indications

PURPOSE

For relief of symptoms related to minor gastritis, indigestion, cramps, and food sensitivities.

Dosage

Unless otherwise prescribed, adults take 15-20 drops, 3 times per day in water or herbal tea. For pediatric dosages, consult your practitioner.

Warning

If symptoms persist, contact a licensed practitioner. If you have known sensitivity to any of the ingredients, please consult your licensed practitioner before use. If you are pregnant or nursing a baby, seek the advice of a health care professional before use.

Keep out of the reach of children.

STORAGE AND HANDLING

Protect from light and heat.

Tamper Evident

Do not use this product if tamper evident strip is broken or removed from base of cap.

QUESTIONS

To report adverse events, contact BioResource at 321B Blodgett Street, Cotati, CA 94931

Distributed by:
BioResource Inc.
Cotati, CA 94931
Made in Germany

Manufactured by:
PEKANA® GmbH
D-88353 Kisslegg

PRINCIPAL DISPLAY PANEL - 100 ml Bottle Box

LivCalm
Oral Drops

Homeopathic Medicine

For relief of symptoms
related to minor gastritis,
indigestion, cramps,
and food sensitivities

3.34 FL OZ
(100 ml)

PEKANA®